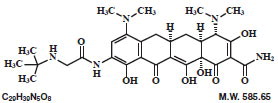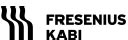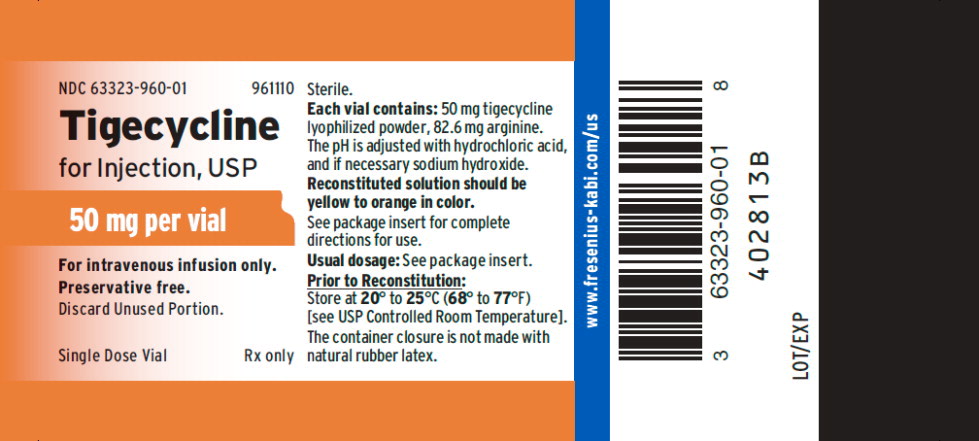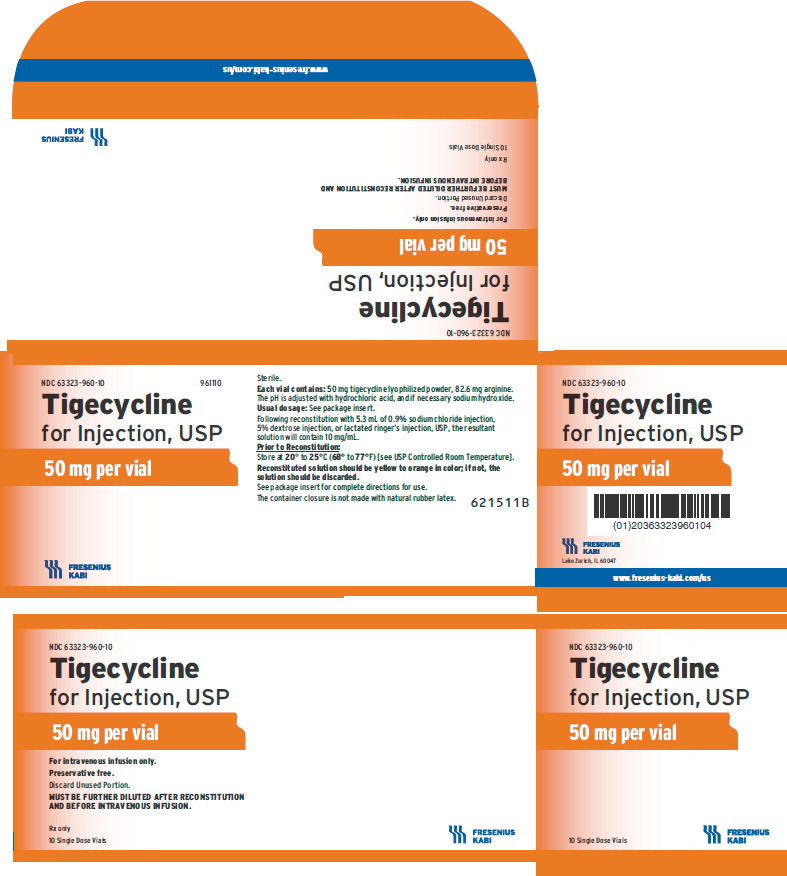 DRUG LABEL: Tigecycline
NDC: 63323-960 | Form: INJECTION, POWDER, LYOPHILIZED, FOR SOLUTION
Manufacturer: Fresenius Kabi USA, LLC
Category: prescription | Type: HUMAN PRESCRIPTION DRUG LABEL
Date: 20240220

ACTIVE INGREDIENTS: TIGECYCLINE 50 mg/5 mL
INACTIVE INGREDIENTS: ARGININE 82.6 mg/5 mL

HIGHLIGHTS OF PRESCRIBING INFORMATION

These highlights do not include all the information needed to use TIGECYCLINE FOR INJECTION safely and effectively. See full prescribing information for TIGECYCLINE FOR INJECTION.
TIGECYCLINE for injection, for intravenous use
Initial U.S. Approval: 2005

WARNING: ALL-CAUSE MORTALITY

See full prescribing information for complete boxed warning.

All-cause mortality was higher in patients treated with tigecycline for injection than comparators in a meta-analysis of clinical trials. The cause of this mortality risk difference of 0.6% (95% CI 0.1, 1.2) has not been established. Tigecycline for injection should be reserved for use in situations when alternative treatments are not suitable (1.4, 5.1, 5.2, 6.1).

1 INDICATIONS AND USAGE

Tigecycline for injection is a tetracycline class antibacterial indicated in patients 18 years of age and older for:

- Complicated skin and skin structure infections (1.1)
- Complicated intra-abdominal infections (1.2)
- Community-acquired bacterial pneumonia (1.3)

Limitations of Use: Tigecycline for injection is not indicated for treatment of diabetic foot infection or hospital-acquired pneumonia, including ventilator-associated pneumonia. (1.4)

To reduce the development of drug-resistant bacteria and maintain the effectiveness of tigecycline for injection and other antibacterial drugs, tigecycline for injection should be used only to treat infections that are proven or strongly suspected to be caused by bacteria. (1.5)

2 DOSAGE AND ADMINISTRATION

- Initial dose of 100 mg, followed by 50 mg every 12 hours administered intravenously over approximately 30 to 60 minutes. (2.1)
- Severe hepatic impairment (Child Pugh C): Initial dose of 100 mg followed by 25 mg every 12 hours. (2.2)

3 DOSAGE FORMS AND STRENGTHS

For Injection: 50 mg, lyophilized powder for reconstitution in a single dose 10 mL vial. (3)

4 CONTRAINDICATIONS

Known hypersensitivity to tigecycline. (4)

5 WARNINGS AND PRECAUTIONS

- All-Cause Mortality: A meta-analysis of Phase 3 and 4 clinical trials demonstrated an increase in all-cause mortality in tigecycline-treated patients compared to controls with a risk difference of 0.6% (95% CI 0.1, 1.2). The cause of this increase has not been established. An increase was also seen in a meta-analysis limited to the approved indications [0.6% (95% CI 0, 1.2)]. The greatest difference in mortality was seen in tigecycline-treated patients with ventilator-associated pneumonia. (5.1, 5.2)
- Anaphylactic Reactions: have been reported with tigecycline, and may be life-threatening. Avoid use in patients with known hypersensitivity to tetracyclines. (5.3)
- Hepatic Adverse Effects: have been reported with tigecycline. Patients who develop abnormal liver function tests during tigecycline therapy should be monitored for evidence of worsening hepatic function and evaluated for risk/benefit of continuing tigecycline therapy. (5.4)
- Pancreatitis: including fatalities, has been reported with tigecycline. If pancreatitis is suspected, then consider stopping tigecycline. (5.5)
- Fetal Harm: Tigecycline may cause fetal harm when administered to a pregnant woman. (5.6)
- Tooth Discoloration: The use of tigecycline during tooth development may cause permanent discoloration of the teeth. (5.7)
- Clostridium difficile-Associated Diarrhea (CDAD): evaluate if diarrhea occurs. (5.8)

6 ADVERSE REACTIONS

The most common adverse reactions (incidence > 5%) are nausea, vomiting, diarrhea, abdominal pain, headache, and increased SGPT. (6.1)

To report SUSPECTED ADVERSE REACTIONS, contact Fresenius Kabi USA, LLC at 1-800-551-7176 or FDA at 1-800-FDA-1088 or www.fda.gov/medwatch.

7 DRUG INTERACTIONS

Suitable anticoagulation test should be monitored if tigecycline is administered to patients receiving warfarin. (7.1)

8 USE IN SPECIFIC POPULATIONS

Pediatrics: Use in patients under 18 years of age is not recommended. Pediatric trials were not conducted because of the higher risk of mortality seen in adult trials. (8.4)

FULL PRESCRIBING INFORMATION

WARNING: ALL-CAUSE MORTALITY

An increase in all-cause mortality has been observed in a meta-analysis of Phase 3 and 4 clinical trials in tigecycline-treated patients versus comparator. The cause of this mortality risk difference of 0.6% (95% CI 0.1, 1.2) has not been established. Tigecycline should be reserved for use in situations when alternative treatments are not suitable [see Indications and Usage (1.4), Warnings and Precautions (5.1, 5.2) and Adverse Reactions (6.1)].

1 INDICATIONS AND USAGE

1.1 Complicated Skin and Skin Structure Infections

Tigecycline for injection is indicated in patients 18 years of age and older for the treatment of complicated skin and skin structure infections caused by susceptible isolates of Escherichia coli, Enterococcus faecalis (vancomycin-susceptible isolates), Staphylococcus aureus (methicillin-susceptible and -resistant isolates), Streptococcus agalactiae, Streptococcus anginosus grp. (includes S. anginosus, S. intermedius, and S. constellatus), Streptococcus pyogenes, Enterobacter cloacae, Klebsiella pneumoniae, and Bacteroides fragilis.

1.2 Complicated Intra-abdominal Infections

Tigecycline for injection is indicated in patients 18 years of age and older for the treatment of complicated intra-abdominal infections caused by susceptible isolates of Citrobacter freundii, Enterobacter cloacae, Escherichia coli, Klebsiella oxytoca, Klebsiella pneumoniae, Enterococcus faecalis (vancomycin-susceptible isolates), Staphylococcus aureus (methicillin-susceptible and -resistant isolates), Streptococcus anginosus grp. (includes S. anginosus, S. intermedius, and S. constellatus), Bacteroides fragilis, Bacteroides thetaiotaomicron, Bacteroides uniformis, Bacteroides vulgatus, Clostridium perfringens, and Peptostreptococcus micros.

1.3 Community-Acquired Bacterial Pneumonia

Tigecycline for injection is indicated in patients 18 years of age and older for the treatment of community-acquired bacterial pneumonia caused by susceptible isolates of Streptococcus pneumoniae (penicillin-susceptible isolates), including cases with concurrent bacteremia, Haemophilus influenzae, and Legionella pneumophila.

1.4 Limitations of Use

Tigecycline for injection is not indicated for the treatment of diabetic foot infections. A clinical trial failed to demonstrate non-inferiority of tigecycline for injection for treatment of diabetic foot infections.

Tigecycline for injection is not indicated for the treatment of hospital-acquired or ventilator-associated pneumonia. In a comparative clinical trial, greater mortality and decreased efficacy were reported in tigecycline-treated patients [see Warnings and Precautions (5.2)].

1.5 Usage

To reduce the development of drug-resistant bacteria and maintain the effectiveness of tigecycline and other antibacterial drugs, tigecycline for injection should be used only to treat infections that are proven or strongly suspected to be caused by susceptible bacteria. When culture and susceptibility information are available, they should be considered in selecting or modifying antibacterial therapy. In the absence of such data, local epidemiology and susceptibility patterns may contribute to the empiric selection of therapy.
Appropriate specimens for bacteriological examination should be obtained in order to isolate and identify the causative organisms and to determine their susceptibility to tigecycline. Tigecycline for injection may be initiated as empiric monotherapy before results of these tests are known.

2 DOSAGE AND ADMINISTRATION

2.1 Recommended Adult Dosage

The recommended dosage regimen for tigecycline for injection is an initial dose of 100 mg, followed by 50 mg every 12 hours. Intravenous infusions of tigecycline for injection should be administered over approximately 30 to 60 minutes every 12 hours. The recommended duration of treatment with tigecycline for injection for complicated skin and skin structure infections or for complicated intra-abdominal infections is 5 to 14 days.
The recommended duration of treatment with tigecycline for injection for community-acquired bacterial pneumonia is 7 to 14 days. The duration of therapy should be guided by the severity and site of the infection and the patient’s clinical and bacteriological progress.

2.2 Dosage in Patients with Hepatic Impairment

No dosage adjustment is warranted in patients with mild to moderate hepatic impairment (Child Pugh A and Child Pugh B). In patients with severe hepatic impairment (Child Pugh C), the initial dose of tigecycline for injection should be 100 mg followed by a reduced maintenance dose of 25 mg every 12 hours. Patients with severe hepatic impairment (Child Pugh C) should be treated with caution and monitored for treatment response [see Clinical Pharmacology (12.3) and Use in Specific Populations (8.6)].

2.3 Dosage in Pediatric Patients

The safety and efficacy of the proposed pediatric dosing regimens have not been evaluated due to the observed increase in mortality associated with tigecycline in adult patients. Avoid use of tigecycline in pediatric patients unless no alternative antibacterial drugs are available. Under these circumstances, the following doses are suggested:

- Pediatric patients aged 8 to 11 years should receive 1.2 mg/kg of tigecycline every 12 hours intravenously to a maximum dose of 50 mg of tigecycline every 12 hours.
- Pediatric patients aged 12 to 17 years should receive 50 mg of tigecycline every 12 hours.

The proposed pediatric doses of tigecycline were chosen based on exposures observed in pharmacokinetic trials, which included small numbers of pediatric patients [see Use in Specific Populations (8.4) and Clinical Pharmacology (12.3)].

There are no data to provide dosing recommendations in pediatric patients with hepatic impairment.

2.4 Preparation and Administration

Each vial of tigecycline for injection should be reconstituted with 5.3 mL of 0.9% Sodium Chloride Injection, USP, 5% Dextrose Injection, USP, or Lactated Ringer's Injection, USP to achieve a concentration of 10 mg/mL of tigecycline. (Note: Each vial contains a 6% overage. Thus, 5 mL of reconstituted solution is equivalent to 50 mg of the drug.) The vial should be gently swirled until the drug dissolves. Reconstituted solution must be transferred and further diluted for intravenous infusion. Withdraw 5 mL of the reconstituted solution from the vial and add to a 100 mL intravenous bag for infusion (for a 100 mg dose, reconstitute two vials; for a 50 mg dose, reconstitute one vial). The maximum concentration in the intravenous bag should be 1 mg/mL. The reconstituted solution should be yellow to orange in color; if not, the solution should be discarded. Parenteral drug products should be inspected visually for particulate matter and discoloration (e.g., green or black) prior to administration. Once reconstituted, tigecycline for injection may be stored at room temperature (not to exceed 25°C/77°F) for up to 24 hours (up to 6 hours in the vial and the remaining time in the intravenous bag). If the storage conditions exceed 25°C (77°F) after reconstitution, tigecycline should be used immediately. Alternatively, tigecycline for injection mixed with 0.9% Sodium Chloride Injection, USP or 5% Dextrose Injection, USP may be stored refrigerated at 2° to 8°C (36° to 46°F) for up to 48 hours following immediate transfer of the reconstituted solution into the intravenous bag.

Tigecycline for injection may be administered intravenously through a dedicated line or through a Y-site. If the same intravenous line is used for sequential infusion of several drugs, the line should be flushed before and after infusion of tigecycline for injection with 0.9% Sodium Chloride Injection, USP, 5% Dextrose Injection, USP or Lactated Ringer’s Injection, USP. Injection should be made with an infusion solution compatible with tigecycline and with any other drug(s) administered via this common line.

2.5 Drug Compatibilities

Compatible intravenous solutions include 0.9% Sodium Chloride Injection, USP, 5% Dextrose Injection, USP, and Lactated Ringer’s Injection, USP. When administered through a Y-site, tigecycline for injection is compatible with the following drugs or diluents when used with either 0.9% Sodium Chloride Injection, USP or 5% Dextrose Injection, USP: amikacin, dobutamine, dopamine HCl, gentamicin, Lactated Ringer’s, lidocaine HCl, metoclopramide, morphine, norepinephrine, potassium chloride, propofol (tested with 5% Dextrose Injection, USP only), ranitidine HCl, theophylline, and tobramycin.

2.6 Drug Incompatibilities

The following drugs should not be administered simultaneously through the same Y-site as tigecycline for injection: amphotericin B, amphotericin B lipid complex, diazepam, esomeprazole, haloperidol and omeprazole.

3 DOSAGE FORMS AND STRENGTHS

For Injection: Each single dose 10 mL glass vial contains 50 mg of tigecycline for injection, USP as an orange lyophilized powder for reconstitution.

4 CONTRAINDICATIONS

Tigecycline for injection is contraindicated for use in patients who have known hypersensitivity to tigecycline. Reactions have included anaphylactic reactions [see Warnings and Precautions (5.3) and Adverse Reactions (6.2)].

5 WARNINGS AND PRECAUTIONS

5.1 All-Cause Mortality

An increase in all-cause mortality has been observed in a meta-analysis of Phase 3 and 4 clinical trials in tigecycline-treated patients versus comparator-treated patients. In all 13 Phase 3 and 4 trials that included a comparator, death occurred in 4.0% (150/3,788) of patients receiving tigecycline and 3.0% (110/3,646) of patients receiving comparator drugs. In a pooled analysis of these trials, based on a random effects model by trial weight, the adjusted risk difference of all-cause mortality was 0.6% (95% CI 0.1, 1.2) between tigecycline and comparator-treated patients. An analysis of mortality in all trials conducted for approved indications (cSSSI, cIAI, and CABP), including post-market trials showed an adjusted mortality rate of 2.5% (66/2,640) for tigecycline and 1.8% (48/2,628) for comparator, respectively. The adjusted risk difference for mortality stratified by trial weight was 0.6% (95% CI 0.0, 1.2).
The cause of this mortality difference has not been established. Generally, deaths were the result of worsening infection, complications of infection or underlying co-morbidities. Tigecycline should be reserved for use in situations when alternative treatments are not suitable [see Boxed Warning, Indications and Usage (1.4), Warnings and Precautions (5.2) and Adverse Reactions (6.1)].

5.2 Mortality Imbalance and Lower Cure Rates in Hospital-Acquired Pneumonia

A trial of patients with hospital acquired, including ventilator-associated, pneumonia failed to demonstrate the efficacy of tigecycline. In this trial, patients were randomized to receive tigecycline (100 mg initially, then 50 mg every 12 hours) or a comparator. In addition, patients were allowed to receive specified adjunctive therapies. The sub-group of patients with ventilator-associated pneumonia who received tigecycline had lower cure rates (47.9% versus 70.1% for the clinically evaluable population).

In this trial, greater mortality was seen in patients with ventilator-associated pneumonia who received tigecycline (25/131 [19.1%] versus 15/122 [12.3%] in comparator-treated patients) [see Adverse Reactions (6.1)]. Particularly high mortality was seen among tigecycline-treated patients with ventilator-associated pneumonia and bacteremia at baseline (9/18 [50.0%] versus 1/13 [7.7%] in comparator-treated patients).

5.3 Anaphylactic Reactions

Anaphylactic reactions have been reported with nearly all antibacterial agents, including tigecycline, and may be life-threatening. Tigecycline is structurally similar to tetracycline-class antibiotics and should be avoided in patients with known hypersensitivity to tetracycline-class antibiotics.

5.4 Hepatic Adverse Effects

Increases in total bilirubin concentration, prothrombin time and transaminases have been seen in patients treated with tigecycline. Isolated cases of significant hepatic dysfunction and hepatic failure have been reported in patients being treated with tigecycline. Some of these patients were receiving multiple concomitant medications. Patients who develop abnormal liver function tests during tigecycline therapy should be monitored for evidence of worsening hepatic function and evaluated for risk/benefit of continuing tigecycline therapy. Hepatic dysfunction may occur after the drug has been discontinued.

5.5 Pancreatitis

Acute pancreatitis, including fatal cases, has occurred in association with tigecycline treatment. The diagnosis of acute pancreatitis should be considered in patients taking tigecycline who develop clinical symptoms, signs, or laboratory abnormalities suggestive of acute pancreatitis. Cases have been reported in patients without known risk factors for pancreatitis. Patients usually improve after tigecycline discontinuation. Consideration should be given to the cessation of the treatment with tigecycline in cases suspected of having developed pancreatitis [see Adverse Reactions (6.2)].

5.6 Fetal Harm

Tigecycline may cause fetal harm when administered to a pregnant woman. If the patient becomes pregnant while taking tigecycline, the patient should be apprised of the potential hazard to the fetus. Results of animal studies indicate that tigecycline crosses the placenta and is found in fetal tissues. Decreased fetal weights in rats and rabbits (with associated delays in ossification) and fetal loss in rabbits have been observed with tigecycline [see Use in Specific Populations (8.1)].

5.7 Tooth Discoloration

The use of tigecycline during tooth development (last half of pregnancy, infancy, and childhood to the age of 8 years) may cause permanent discoloration of the teeth (yellow-gray-brown). Results of studies in rats with tigecycline have shown bone discoloration. Tigecycline should not be used during tooth development unless other drugs are not likely to be effective or are contraindicated.

5.8 Clostridium difficile -Associated Diarrhea

Clostridium difficile associated diarrhea (CDAD) has been reported with use of nearly all antibacterial agents, including tigecycline, and may range in severity from mild diarrhea to fatal colitis. Treatment with antibacterial agents alters the normal flora of the colon leading to overgrowth of C. difficile.

C. difficile produces toxins A and B which contribute to the development of CDAD. Hypertoxin producing strains of C. difficile cause increased morbidity and mortality, as these infections can be refractory to antimicrobial therapy and may require colectomy. CDAD must be considered in all patients who present with diarrhea following antibiotic use. Careful medical history is necessary since CDAD has been reported to occur over two months after the administration of antibacterial agents.

If CDAD is suspected or confirmed, ongoing antibiotic use not directed against C. difficile may need to be discontinued. Appropriate fluid and electrolyte management, protein supplementation, antibiotic treatment of C. difficile, and surgical evaluation should be instituted as clinically indicated.

5.9 Sepsis/Septic Shock in Patients with Intestinal Perforation

Monotherapy with tigecycline should be avoided in patients with complicated intra-abdominal infections (cIAI) secondary to clinically apparent intestinal perforation. In cIAI studies (n=1,642), 6 patients treated with tigecycline and 2 patients treated with imipenem/cilastatin presented with intestinal perforations and developed sepsis/septic shock. The 6 patients treated with tigecycline had higher APACHE II scores (median = 13) versus the 2 patients treated with imipenem/cilastatin (APACHE II scores = 4 and 6). Due to differences in baseline APACHE II scores between treatment groups and small overall numbers, the relationship of this outcome to treatment cannot be established.

5.10 Tetracycline-Class Adverse Effects

Tigecycline is structurally similar to tetracycline-class antibacterial drugs and may have similar adverse effects. Such effects may include: photosensitivity, pseudotumor cerebri, and anti-anabolic action (which has led to increased BUN, azotemia, acidosis, and hyperphosphatemia).

5.11 Development of Drug-Resistant Bacteria

Prescribing tigecycline for injection in the absence of a proven or strongly suspected bacterial infection is unlikely to provide benefit to the patient and increases the risk of the development of drug-resistant bacteria.

6 ADVERSE REACTIONS

The following serious adverse reactions are described elsewhere in the labeling:

- All-Cause Mortality [see Boxed Warning and Warnings and Precautions (5.1)]
- Mortality Imbalance and Lower Cure Rates in Hospital-Acquired Pneumonia [see Warnings and Precautions (5.2)]
- Anaphylaxis [Warning and Precautions (5.3)]
- Hepatic Adverse Effects [Warnings and Precautions (5.4)]
- Pancreatitis [Warnings and Precautions (5.5)]

6.1 Clinical Trials Experience

Because clinical trials are conducted under widely varying conditions, adverse reaction rates observed in the clinical trials of a drug cannot be directly compared to rates in the clinical trials of another drug and may not reflect the rates observed in practice.

In clinical trials, 2,514 patients were treated with tigecycline. Tigecycline was discontinued due to adverse reactions in 7% of patients compared to 6% for all comparators. Table 1 shows the incidence of adverse reactions through test of cure reported in ≥ 2% of patients in these trials.

Table 1. Incidence (%) of Adverse Reactions Through Test of Cure

Reported in ≥ 2% of Patients Treated in Clinical Studies

Body System Adverse Reactions | Tigecycline (N=2,514) | Comparatorsa (N=2,307)
Body as a Whole
Abdominal pain | 6 | 4
Abscess | 2 | 2
Asthenia | 3 | 2
Headache | 6 | 7
Infection | 7 | 5
Cardiovascular System
Phlebitis | 3 | 4
Digestive System
Diarrhea | 12 | 11
Dyspepsia | 2 | 2
Nausea | 26 | 13
Vomiting | 18 | 9
Hemic and Lymphatic System
Anemia | 5 | 6
Metabolic and Nutritional
Alkaline Phosphatase Increased | 3 | 3
Amylase Increased | 3 | 2
Bilirubinemia | 2 | 1
BUN Increased | 3 | 1
Healing Abnormal | 3 | 2
Hyponatremia | 2 | 1
Hypoproteinemia | 5 | 3
SGOT Increasedb | 4 | 5
SGPT Increasedb | 5 | 5
Respiratory System
Pneumonia | 2 | 2
Nervous System
Dizziness | 3 | 3
Skin and Appendages
Rash | 3 | 4

a Vancomycin/Aztreonam, Imipenem/Cilastatin, Levofloxacin, Linezolid.

b LFT abnormalities in tigecycline-treated patients were reported more frequently in the post therapy period

than those in comparator-treated patients, which occurred more often on therapy.

In all 13 Phase 3 and 4 trials that included a comparator, death occurred in 4.0% (150/3,788) of patients receiving tigecycline and 3.0% (110/3,646) of patients receiving comparator drugs. In a pooled analysis of these trials, based on a random effects model by trial weight, an adjusted risk difference of all-cause mortality was 0.6% (95% CI 0.1, 1.2) between tigecycline and comparator-treated patients (see Table 2). The cause of the imbalance has not been established. Generally, deaths were the result of worsening infection, complications of infection or underlying co-morbidities.

Table 2. Patients with Outcome of Death by Infection Type

 | Tigecycline |  | Comparator |  | Risk Difference*
Infection Type | n/N | % | n/N | % | % (95% CI)
cSSSI | 12/834 | 1.4 | 6/813 | 0.7 | 0.7 (-0.3, 1.7)
cIAI | 42/1,382 | 3.0 | 31/1,393 | 2.2 | 0.8 (-0.4, 2.0)
CAP | 12/424 | 2.8 | 11/422 | 2.6 | 0.2 (-2.0, 2.4)
HAP | 66/467 | 14.1 | 57/467 | 12.2 | 1.9 (-2.4, 6.3)
Non-VAPa | 41/336 | 12.2 | 42/345 | 12.2 | 0.0 (-4.9, 4.9)
VAPa | 25/131 | 19.1 | 15/122 | 12.3 | 6.8 (-2.1, 15.7)
RP | 11/128 | 8.6 | 2/43 | 4.7 | 3.9 (-4.0, 11.9)
DFI | 7/553 | 1.3 | 3/508 | 0.6 | 0.7 (-0.5, 1.8)
Overall Adjusted | 150/3,788 | 4.0 | 110/3,646 | 3.0 | 0.6 (0.1, 1.2)**

CAP = Community-acquired pneumonia; cIAI = Complicated intra-abdominal infections;

cSSSI = Complicated skin and skin structure infections; HAP = Hospital-acquired pneumonia;

VAP = Ventilator-associated pneumonia; RP = Resistant pathogens; DFI = Diabetic foot infections.

* The difference between the percentage of patients who died in tigecycline and comparator treatment groups.

The 95% CI for each infection type was calculated using the normal approximation method without

continuity correction.

** Overall adjusted (random effects model by trial weight) risk difference estimate and 95% CI.

a These are subgroups of the HAP population.

Note: The studies include 300, 305, 900 (cSSSI), 301, 306, 315, 316, 400 (cIAI), 308 and 313 (CAP), 311 (HAP), 307 [Resistant gram-positive pathogen study in patients with MRSA or Vancomycin-Resistant Enterococcus (VRE)], and 319 (DFI with and without osteomyelitis).

An analysis of mortality in all trials conducted for approved indications - cSSSI, cIAI, and CABP, including post-market trials (one in cSSSI and two in cIAI) - showed an adjusted mortality rate of 2.5% (66/2,640) for tigecycline and 1.8% (48/2,628) for comparator, respectively. The adjusted risk difference for mortality stratified by trial weight was 0.6% (95% CI 0.0, 1.2).

In comparative clinical studies, infection-related serious adverse reactions were more frequently reported for subjects treated with tigecycline (7%) versus comparators (6%). Serious adverse reactions of sepsis/septic shock were more frequently reported for subjects treated with tigecycline (2%) versus comparators (1%). Due to baseline differences between treatment groups in this subset of patients, the relationship of this outcome to treatment cannot be established [see Warnings and Precautions (5.9)].

The most common adverse reactions were nausea and vomiting which generally occurred during the first 1 to 2 days of therapy. The majority of cases of nausea and vomiting associated with tigecycline and comparators were either mild or moderate in severity. In patients treated with tigecycline, nausea incidence was 26% (17% mild, 8% moderate, 1% severe) and vomiting incidence was 18% (11% mild, 6% moderate, 1% severe).

In patients treated for complicated skin and skin structure infections (cSSSI), nausea incidence was 35% for tigecycline and 9% for vancomycin/aztreonam; vomiting incidence was 20% for tigecycline and 4% for vancomycin/aztreonam. In patients treated for complicated intra-abdominal infections (cIAI), nausea incidence was 25% for tigecycline and 21% for imipenem/cilastatin; vomiting incidence was 20% for tigecycline and 15% for imipenem/cilastatin. In patients treated for community-acquired bacterial pneumonia (CABP), nausea incidence was 24% for tigecycline and 8% for levofloxacin; vomiting incidence was 16% for tigecycline and 6% for levofloxacin.

Discontinuation from tigecycline was most frequently associated with nausea (1%) and vomiting (1%). For comparators, discontinuation was most frequently associated with nausea (< 1%).

The following adverse reactions were reported (< 2%) in patients receiving tigecycline in clinical studies:

Body as a Whole: injection site inflammation, injection site pain, injection site reaction, septic shock, allergic reaction, chills, injection site edema, injection site phlebitis

Cardiovascular System: thrombophlebitis

Digestive System: anorexia, jaundice, abnormal stools

Metabolic/Nutritional System: increased creatinine, hypocalcemia, hypoglycemia

Special Senses: taste perversion

Hemic and Lymphatic System: prolonged activated partial thromboplastin time (aPTT), prolonged prothrombin time (PT), eosinophilia, increased international normalized ratio (INR), thrombocytopenia

Skin and Appendages: pruritus

Urogenital System: vaginal moniliasis, vaginitis, leukorrhea

6.2 Post-Marketing Experience

The following adverse reactions have been identified during post-approval use of tigecycline. Because these reactions are reported voluntarily from a population of uncertain size, it is not always possible to reliably estimate their frequency or establish causal relationship to drug exposure.

- anaphylactic reactions
- acute pancreatitis
- hepatic cholestasis, and jaundice
- severe skin reactions, including Stevens-Johnson Syndrome
- symptomatic hypoglycemia in patients with and without diabetes mellitus

7 DRUG INTERACTIONS

7.1 Warfarin

Prothrombin time or other suitable anticoagulation test should be monitored if tigecycline is administered with warfarin [see Clinical Pharmacology (12.3)].

7.2 Oral Contraceptives

Concurrent use of antibacterial drugs with oral contraceptives may render oral contraceptives less effective.

8 USE IN SPECIFIC POPULATIONS

8.1 Pregnancy

Teratogenic Effects—Pregnancy Category D [see Warnings and Precautions (5.6)]

Tigecycline was not teratogenic in the rat or rabbit. In preclinical safety studies, ^14C-labeled tigecycline crossed the placenta and was found in fetal tissues, including fetal bony structures. The administration of tigecycline was associated with reductions in fetal weights and an increased incidence of skeletal anomalies (delays in bone ossification) at exposures of 5 times and 1 times the human daily dose based on AUC in rats and rabbits, respectively (28 mcg•hr/mL and 6 mcg•hr/mL at 12 and 4 mg/kg/day). An increased incidence of fetal loss was observed at maternotoxic doses in the rabbits with exposure equivalent to human dose.

There are no adequate and well-controlled studies of tigecycline in pregnant women. Tigecycline should be used during pregnancy only if the potential benefit justifies the potential risk to the fetus.

8.3 Nursing Mothers

Results from animal studies using ^14C-labeled tigecycline indicate that tigecycline is excreted readily via the milk of lactating rats. Consistent with the limited oral bioavailability of tigecycline, there is little or no systemic exposure to tigecycline in nursing pups as a result of exposure via maternal milk.

It is not known whether this drug is excreted in human milk. Because many drugs are excreted in human milk, caution should be exercised when tigecycline is administered to a nursing woman [see Warnings and Precautions (5.7)].

8.4 Pediatric Use

Use in patients under 18 years of age is not recommended. Safety and effectiveness in pediatric patients below the age of 18 years have not been established. Because of the increased mortality observed in tigecycline-treated adult patients in clinical trials, pediatric trials of tigecycline to evaluate the safety and efficacy of tigecycline were not conducted.

In situations where there are no other alternative antibacterial drugs, dosing has been proposed for pediatric patients 8 to 17 years of age based on data from pediatric pharmacokinetic studies [see Dosage and Administration (2.3) and Clinical Pharmacology (12.3)].

Because of effects on tooth development, use in patients under 8 years of age is not recommended [see Warnings and Precautions (5.7)].

8.5 Geriatric Use

Of the total number of subjects who received tigecycline in Phase 3 clinical studies (n=2,514), 664 were 65 and over, while 288 were 75 and over. No overall differences in safety or effectiveness were observed between these subjects and younger subjects, but greater sensitivity to adverse events of some older individuals cannot be ruled out.

No significant difference in tigecycline exposure was observed between healthy elderly subjects and younger subjects following a single 100 mg dose of tigecycline [see Clinical Pharmacology (12.3)].

8.6 Hepatic Impairment

No dosage adjustment is warranted in patients with mild to moderate hepatic impairment (Child Pugh A and Child Pugh B). In patients with severe hepatic impairment (Child Pugh C), the initial dose of tigecycline should be 100 mg followed by a reduced maintenance dose of 25 mg every 12 hours. Patients with severe hepatic impairment (Child Pugh C) should be treated with caution and monitored for treatment response [see Clinical Pharmacology (12.3) and Dosage and Administration (2.2)].

10 OVERDOSAGE

No specific information is available on the treatment of overdosage with tigecycline. Intravenous administration of tigecycline at a single dose of 300 mg over 60 minutes in healthy volunteers resulted in an increased incidence of nausea and vomiting. Tigecycline is not removed in significant quantities by hemodialysis.

11 DESCRIPTION

Tigecycline for injection, USP is a tetracycline class antibacterial for intravenous infusion. The chemical name of tigecycline is (4S,4aS,5aR,12aS)-9-[2-(tert-butylamino)acetamido]-4,7-bis(dimethylamino)-1,4,4a,5,5a,6,11,12a-octahydro-3,10,12,12a-tetrahydroxy-1,11-dioxo-2-naphthacenecarboxamide.

The following represents the chemical structure of tigecycline:

Figure 1: Structure of Tigecycline

Tigecycline for injection, USP is an orange lyophilized powder or cake. Each tigecycline single dose 10 mL vial contains 50 mg tigecycline and 82.6 mg of arginine as lyophilized powder for reconstitution for intravenous infusion. The pH is adjusted with hydrochloric acid, and if necessary sodium hydroxide. The product does not contain preservatives.

12 CLINICAL PHARMACOLOGY

12.1 Mechanism of Action

Tigecycline is a tetracycline class antibacterial [see Microbiology (12.4)].

12.2 Pharmacodynamics

Cardiac Electrophysiology

No significant effect of a single intravenous dose of tigecycline 50 mg or 200 mg on QTc interval was detected in a randomized, placebo- and active-controlled four-arm crossover thorough QTc study of 46 healthy subjects.

12.3 Pharmacokinetics

The mean pharmacokinetic parameters of tigecycline after single and multiple intravenous doses based on pooled data from clinical pharmacology studies are summarized in Table 3. Intravenous infusions of tigecycline were administered over approximately 30 to 60 minutes.

Table 3. Mean (CV%) Pharmacokinetic Parameters of Tigecycline

 | Single Dose 100 mg (N=224) | Multiple Dosea 50 mg every 12h (N=103)
Cmax (mcg/mL)b | 1.45 (22%) | 0.87 (27%)
Cmax (mcg/mL)c | 0.90 (30%) | 0.63 (15%)
AUC (mcg•h/mL) | 5.19 (36%) | - -
AUC0-24h (mcg•h/mL) | - - | 4.7 (36%)
Cmin (mcg/mL) | - - | 0.13 (59%)
t½ (h) | 27.1 (53%) | 42.4 (83%)
CL (L/h) | 21.8 (40%) | 23.8 (33%)
CLr (mL/min) | 38.0 (82%) | 51.0 (58%)
Vss (L) | 568 (43%) | 639 (48%)

a 100 mg initially, followed by 50 mg every 12 hours

b 30-minute infusion

c 60-minute infusion

Distribution

The in vitro plasma protein binding of tigecycline ranges from approximately 71% to 89% at concentrations observed in clinical studies (0.1 to 1.0 mcg/mL). The steady-state volume of distribution of tigecycline averaged 500 to 700 L (7 to 9 L/kg), indicating tigecycline is extensively distributed beyond the plasma volume and into the tissues.

Following the administration of tigecycline 100 mg followed by 50 mg every 12 hours to 33 healthy volunteers, the tigecycline AUC0-12h (134 mcg•h/mL) in alveolar cells was approximately 78-fold higher than the AUC0-12h in the serum, and the AUC0-12h (2.28 mcg•h/mL) in epithelial lining fluid was approximately 32% higher than the AUC0-12h in serum. The AUC0-12h (1.61 mcg•h/mL) of tigecycline in skin blister fluid was approximately 26% lower than the AUC0-12h in the serum of 10 healthy subjects.

In a single-dose study, tigecycline 100 mg was administered to subjects prior to undergoing elective surgery or medical procedure for tissue extraction. Concentrations at 4 hours after tigecycline administration were higher in gallbladder (38-fold, n=6), lung (3.7-fold, n=5), and colon (2.3-fold, n=6), and lower in synovial fluid (0.58-fold, n=5), and bone (0.35-fold, n=6) relative to serum. The concentration of tigecycline in these tissues after multiple doses has not been studied.

Elimination

Metabolism

Tigecycline is not extensively metabolized. In vitro studies with tigecycline using human liver microsomes, liver slices, and hepatocytes led to the formation of only trace amounts of metabolites. In healthy male volunteers receiving ^14C-tigecycline, tigecycline was the primary ^14C-labeled material recovered in urine and feces, but a glucuronide, an N-acetyl metabolite, and a tigecycline epimer (each at no more than 10% of the administered dose) were also present.
Tigecycline is a substrate of P-glycoprotein (P-gp) based on an in vitro study using a cell line overexpressing P-gp. The potential contribution of P-gp-mediated transport to the in vivo disposition of tigecycline is not known.

Excretion

The recovery of total radioactivity in feces and urine following administration of ^14C -tigecycline indicates that 59% of the dose is eliminated by biliary/fecal excretion, and 33% is excreted in urine. Approximately 22% of the total dose is excreted as unchanged tigecycline in urine. Overall, the primary route of elimination for tigecycline is biliary excretion of unchanged tigecycline and its metabolites. Glucuronidation and renal excretion of unchanged tigecycline are secondary routes.

Specific Populations

Hepatic Impairment

In a study comparing 10 patients with mild hepatic impairment (Child Pugh A), 10 patients with moderate hepatic impairment (Child Pugh B), and 5 patients with severe hepatic impairment (Child Pugh C) to 23 age and weight matched healthy control subjects, the single-dose pharmacokinetic disposition of tigecycline was not altered in patients with mild hepatic impairment. However, systemic clearance of tigecycline was reduced by 25% and the half-life of tigecycline was prolonged by 23% in patients with moderate hepatic impairment (Child Pugh B). Systemic clearance of tigecycline was reduced by 55%, and the half-life of tigecycline was prolonged by 43% in patients with severe hepatic impairment (Child Pugh C). Dosage adjustment is necessary in patients with severe hepatic impairment (Child Pugh C) [see Use in Specific Populations (8.6) and Dosage and Administration (2.2)].

Renal Impairment

A single dose study compared 6 subjects with severe renal impairment (creatinine clearance < 30 mL/min), 4 end stage renal disease (ESRD) patients receiving tigecycline 2 hours before hemodialysis, 4 ESRD patients receiving tigecycline 1 hour after hemodialysis, and 6 healthy control subjects. The pharmacokinetic profile of tigecycline was not significantly altered in any of the renally impaired patient groups, nor was tigecycline removed by hemodialysis. No dosage adjustment of tigecycline is necessary in patients with renal impairment or in patients undergoing hemodialysis.

Geriatric Patients

No significant differences in pharmacokinetics were observed between healthy elderly subjects (n=15, age 65 to 75; n=13, age > 75) and younger subjects (n=18) receiving a single 100 mg dose of tigecycline. Therefore, no dosage adjustment is necessary based on age [see Use in Specific Populations (8.5)].

Pediatric Patients

A single-dose safety, tolerability, and pharmacokinetic study of tigecycline in pediatric patients aged 8 to 16 years who recently recovered from infections was conducted. The doses administered were 0.5, 1, or 2 mg/kg. The study showed that for children aged 12 to 16 years (n = 16) a dosage of 50 mg twice daily would likely result in exposures comparable to those observed in adults with the approved dosing regimen. Large variability observed in children aged 8 to 11 years of age (n = 8) required additional study to determine the appropriate dosage.

A subsequent tigecycline dose-finding study was conducted in 8 to 11 year old patients with cIAI, cSSSI, or CABP. The doses of tigecycline studied were 0.75 mg/kg (n = 17), 1 mg/kg (n = 21), and 1.25 mg/kg (n=20). This study showed that for children aged 8 to 11 years, a 1.2 mg/kg dose would likely result in exposures comparable to those observed in adults resulting with the approved dosing regimen [see Dosage and Administration (2.3)].

Gender

In a pooled analysis of 38 women and 298 men participating in clinical pharmacology studies, there was no significant difference in the mean (± SD) tigecycline clearance between women (20.7 ± 6.5 L/h) and men (22.8 ± 8.7 L/h). Therefore, no dosage adjustment is necessary based on gender.

Race

In a pooled analysis of 73 Asian subjects, 53 Black subjects, 15 Hispanic subjects, 190 White subjects, and 3 subjects classified as “other” participating in clinical pharmacology studies, there was no significant difference in the mean (± SD) tigecycline clearance among the Asian subjects (28.8 ± 8.8 L/h), Black subjects (23 ± 7.8 L/h), Hispanic subjects (24.3 ± 6.5 L/h), White subjects (22.1 ± 8.9 L/h), and “other” subjects (25 ± 4.8 L/h). Therefore, no dosage adjustment is necessary based on race.

Drug Interaction Studies

Digoxin

Tigecycline (100 mg followed by 50 mg every 12 hours) and digoxin (0.5 mg followed by 0.25 mg, orally, every 24 hours) were co-administered to healthy subjects in a drug interaction study. Tigecycline slightly decreased the Cmax of digoxin by 13%, but did not affect the AUC or clearance of digoxin. This small change in Cmax did not affect the steady-state pharmacodynamic effects of digoxin as measured by changes in ECG intervals. In addition, digoxin did not affect the pharmacokinetic profile of tigecycline. Therefore, no dosage adjustment of either drug is necessary when tigecycline is administered with digoxin.

Warfarin

Concomitant administration of tigecycline (100 mg followed by 50 mg every 12 hours) and warfarin (25 mg single-dose) to healthy subjects resulted in a decrease in clearance of R-warfarin and S-warfarin by 40% and 23%, an increase in Cmax by 38% and 43% and an increase in AUC by 68% and 29%, respectively. Tigecycline did not significantly alter the effects of warfarin on INR. In addition, warfarin did not affect the pharmacokinetic profile of tigecycline. However, prothrombin time or other suitable anticoagulation test should be monitored if tigecycline is administered with warfarin.

In vitro studies in human liver microsomes indicate that tigecycline does not inhibit metabolism mediated by any of the following 6 cytochrome P450 (CYP) isoforms: 1A2, 2C8, 2C9, 2C19, 2D6, and 3A4. Therefore, tigecycline is not expected to alter the metabolism of drugs metabolized by these enzymes. In addition, because tigecycline is not extensively metabolized, clearance of tigecycline is not expected to be affected by drugs that inhibit or induce the activity of these CYP450 isoforms.

In vitro studies using Caco-2 cells indicate that tigecycline does not inhibit digoxin flux, suggesting that tigecycline is not a P-glycoprotein (P-gp) inhibitor. This in vitro information is consistent with the lack of effect of tigecycline on digoxin clearance noted in the in vivo drug interaction study described above.

Tigecycline is a substrate of P-gp based on an in vitro study using a cell line overexpressing P-gp. The potential contribution of P-gp-mediated transport to the in vivo disposition of tigecycline is not known. Coadministration of P-gp inhibitors (e.g., ketoconazole or cyclosporine) or P-gp inducers (e.g., rifampicin) could affect the pharmacokinetics of tigecycline.

12.4 Microbiology

Mechanism of Action

Tigecycline inhibits protein translation in bacteria by binding to the 30S ribosomal subunit and blocking entry of amino-acyl tRNA molecules into the A site of the ribosome. This prevents incorporation of amino acid residues into elongating peptide chains. In general, tigecycline is considered bacteriostatic; however, tigecycline has demonstrated bactericidal activity against isolates of S. pneumoniae and L. pneumophila.

Resistance

To date there has been no cross-resistance observed between tigecycline and other antibacterials. Tigecycline is less affected by the two major tetracycline-resistance mechanisms, ribosomal protection and efflux. Additionally, tigecycline is not affected by resistance mechanisms such as beta-lactamases (including extended spectrum beta-lactamases), target-site modifications, macrolide efflux pumps or enzyme target changes (e.g. gyrase/topoisomerases). However, some ESBL-producing isolates may confer resistance to tigecycline via other resistance mechanisms. Tigecycline resistance in some bacteria (e.g. Acinetobacter calcoaceticus-Acinetobacter baumannii complex) is associated with multi-drug resistant (MDR) efflux pumps.

Interaction with Other Antimicrobials

In vitro studies have not demonstrated antagonism between tigecycline and other commonly used antibacterials.

Antimicrobial Activity

Tigecycline has been shown to be active against most of the following microorganisms, both in vitro and in clinical infections [see Indications and Usage (1)].

Gram-positive bacteria

Enterococcus faecalis (vancomycin-susceptible isolates)

Staphylococcus aureus (methicillin-susceptible and -resistant isolates)

Streptococcus agalactiae

Streptococcus anginosus group (includes S. anginosus, S. intermedius, and S. constellatus)

Streptococcus pneumoniae (penicillin-susceptible isolates)

Streptococcus pyogenes

Gram-negative bacteria

Citrobacter freundii

Enterobacter cloacae

Escherichia coli

Haemophilus influenzae

Klebsiella oxytoca

Klebsiella pneumoniae

Legionella pneumophila

Anaerobic bacteria

Bacteroides fragilis

Bacteroides thetaiotaomicron

Bacteroides uniformis

Bacteroides vulgatus

Clostridium perfringens

Peptostreptococcus micros

The following in vitro data are available, but their clinical significance is unknown. At least

90 percent of the following bacteria exhibit an in vitro minimum inhibitory concentration (MIC) less than or equal to the susceptible breakpoint for tigecycline against isolates of similar genus or organism group. However, the efficacy of tigecycline in treating clinical infections caused by these bacteria has not been established in adequate and well-controlled clinical trials.

Gram-positive bacteria

Enterococcus avium

Enterococcus casseliflavus

Enterococcus faecalis (vancomycin-resistant isolates)

Enterococcus faecium (vancomycin-susceptible and -resistant isolates)

Enterococcus gallinarum

Listeria monocytogenes

Staphylococcus epidermidis (methicillin-susceptible and -resistant isolates)

Staphylococcus haemolyticus

Gram-negative bacteria

Acinetobacter baumannii*

Aeromonas hydrophila

Citrobacter koseri

Enterobacter aerogenes

Haemophilus influenzae (ampicillin-resistant)

Haemophilus parainfluenzae

Pasteurella multocida

Serratia marcescens

Stenotrophomonas maltophilia

Anaerobic bacteria

Bacteroides distasonis

Bacteroides ovatus

Peptostreptococcus spp.

Porphyromonas spp.

Prevotella spp.

Other bacteria

Mycobacterium abscessus

Mycobacterium fortuitum

*There have been reports of the development of tigecycline resistance in Acinetobacter infections seen during the course of standard treatment. Such resistance appears to be attributable to an MDR efflux pump mechanism. While monitoring for relapse of infection is important for all infected patients, more frequent monitoring in this case is suggested. If relapse is suspected, blood and other specimens should be obtained and cultured for the presence of bacteria. All bacterial isolates should be identified and tested for susceptibility to tigecycline and other appropriate antimicrobials.

Susceptibility Testing

For specific information regarding susceptibility test interpretive criteria and associated test methods and quality control standards recognized by FDA for this drug, please see: https://www.fda.gov/STIC.

13 NONCLINICAL TOXICOLOGY

13.1 Carcinogenesis, Mutagenesis, Impairment of Fertility

Lifetime studies in animals have not been performed to evaluate the carcinogenic potential of tigecycline. No mutagenic or clastogenic potential was found in a battery of tests, including in vitro chromosome aberration assay in Chinese hamster ovary (CHO) cells, in vitro forward mutation assay in CHO cells (HGRPT locus), in vitro forward mutation assays in mouse lymphoma cells, and in vivo mouse micronucleus assay. Tigecycline did not affect mating or fertility in rats at exposures up to 5 times the human daily dose based on AUC (28 mcg•hr/mL at 12 mg/kg/day). In female rats, there were no compound-related effects on ovaries or estrous cycles at exposures up to 5 times the human daily dose based on AUC.

13.2 Animal Toxicology and/or Pharmacology

In two week studies, decreased erythrocytes, reticulocytes, leukocytes, and platelets, in association with bone marrow hypocellularity, have been seen with tigecycline at exposures of 8 times and 10 times the human daily dose based on AUC in rats and dogs, (AUC of approximately 50 and 60 mcg•hr/mL at doses of 30 and 12 mg/kg/day) respectively. These alterations were shown to be reversible after two weeks of dosing.

14 CLINICAL STUDIES

14.1 Complicated Skin and Skin Structure Infections

Tigecycline was evaluated in adults for the treatment of complicated skin and skin structure infections (cSSSI) in two randomized, double-blind, active-controlled, multinational, multicenter studies (Studies 300 and 305). These studies compared tigecycline (100 mg intravenous initial dose followed by 50 mg every 12 hours) with vancomycin (1 g intravenous every 12 hours)/aztreonam (2 g intravenous every 12 hours) for 5 to 14 days. Patients with complicated deep soft tissue infections including wound infections and cellulitis (≥ 10 cm, requiring surgery/drainage or with complicated underlying disease), major abscesses, infected ulcers, and burns were enrolled in the studies. The primary efficacy endpoint was the clinical response at the test of cure (TOC) visit in the co-primary populations of the clinically evaluable (CE) and clinical modified intent-to-treat (c-mITT) patients. See Table 4. Clinical cure rates at TOC by pathogen in the microbiologically evaluable patients are presented in Table 5.

Table 4. Clinical Cure Rates from Two Studies in Complicated Skin and Skin Structure Infections after 5 to 14 Days of Therapy

 | Tigecyclinea n/N (%) | Vancomycin/Aztreonamb n/N (%)
Study 300
CE | 165/199 (82.9) | 163/198 (82.3)
c-mITT | 209/277 (75.5) | 200/260 (76.9)
Study 305
CE | 200/223 (89.7) | 201/213 (94.4)
c-mITT | 220/261 (84.3) | 225/259 (86.9)

a 100 mg initially, followed by 50 mg every 12 hours

b Vancomycin (1 g every 12 hours)/Aztreonam (2 g every 12 hours)

Table 5. Clinical Cure Rates by Infecting Pathogen in Microbiologically Evaluable Patients with Complicated Skin and Skin Structure Infectionsa

Pathogen | Tigecycline n/N (%) | Vancomycin/Aztreonam n/N (%)
Escherichia coli | 29/36 (80.6) | 26/30 (86.7)
Enterobacter cloacae | 10/12 (83.3) | 15/15 (100)
Enterococcus faecalis (vancomycin-susceptible only) | 15/21 (71.4) | 19/24 (79.2)
Klebsiella pneumoniae | 12/14 (85.7) | 15/16 (93.8)
Methicillin-susceptible Staphylococcus aureus (MSSA) | 124/137 (90.5) | 113/120 (94.2)
Methicillin-resistant Staphylococcus aureus (MRSA) | 79/95 (83.2) | 46/57 (80.7)
Streptococcus agalactiae | 8/8 (100) | 11/14 (78.6)
Streptococcus anginosus grpb | 17/21 (81.0) | 9/10 (90.0)
Streptococcus pyogenes | 31/32 (96.9) | 24/27 (88.9)
Bacteroides fragilis | 7/9 (77.8) | 4/5 (80.0)

a Two cSSSI pivotal studies and two Resistant Pathogen studies

b Includes Streptococcus anginosus, Streptococcus intermedius, and Streptococcus constellatus

14.2 Complicated Intra-abdominal Infections

Tigecycline was evaluated in adults for the treatment of complicated intra-abdominal infections (cIAI) in two randomized, double-blind, active-controlled, multinational, multicenter studies (Studies 301 and 306). These studies compared tigecycline (100 mg intravenous initial dose followed by 50 mg every 12 hours) with imipenem/cilastatin (500 mg intravenous every 6 hours) for 5 to 14 days. Patients with complicated diagnoses including appendicitis, cholecystitis, diverticulitis, gastric/duodenal perforation, intra-abdominal abscess, perforation of intestine, and peritonitis were enrolled in the studies. The primary efficacy endpoint was the clinical response at the TOC visit for the co-primary populations of the microbiologically evaluable (ME) and the microbiologic modified intent-to-treat (m-mITT) patients. See Table 6. Clinical cure rates at TOC by pathogen in the microbiologically evaluable patients are presented in Table 7.

Table 6. Clinical Cure Rates from Two Studies in Complicated Intra-abdominal Infections after 5 to 14 Days of Therapy

 | Tigecyclinea n/N (%) | Imipenem/Cilastatin b n/N (%)
Study 301
ME | 199/247 (80.6) | 210/255 (82.4)
m-mITT | 227/309 (73.5) | 244/312 (78.2)
Study 306
ME | 242/265 (91.3) | 232/258 (89.9)
m-mITT | 279/322 (86.6) | 270/319 (84.6)

a 100 mg initially, followed by 50 mg every 12 hours

b Imipenem/Cilastatin (500 mg every 6 hours)

Table 7. Clinical Cure Rates by Infecting Pathogen in Microbiologically Evaluable Patients with Complicated Intra-abdominal Infectionsa

Pathogen | Tigecycline n/N (%) | Imipenem/Cilastatin n/N (%)
Citrobacter freundii | 12/16 (75.0) | 3/4 (75.0)
Enterobacter cloacae | 15/17 (88.2) | 16/17 (94.1)
Escherichia coli | 284/336 (84.5) | 297/342 (86.8)
Klebsiella oxytoca | 19/20 (95.0) | 17/19 (89.5)
Klebsiella pneumoniae | 42/47 (89.4) | 46/53 (86.8)
Enterococcus faecalis | 29/38 (76.3) | 35/47 (74.5)
Methicillin-susceptible Staphylococcus aureus (MSSA) | 26/28 (92.9) | 22/24 (91.7)
Methicillin-resistant Staphylococcus aureus (MRSA) | 16/18 (88.9) | 1/3 (33.3)
Streptococcus anginosus grpb | 101/119 (84.9) | 60/79 (75.9)
Bacteroides fragilis | 68/88 (77.3) | 59/73 (80.8)
Bacteroides thetaiotaomicron | 36/41 (87.8) | 31/36 (86.1)
Bacteroides uniformis | 12/17 (70.6) | 14/16 (87.5)
Bacteroides vulgatus | 14/16 (87.5) | 4/6 (66.7)
Clostridium perfringens | 18/19 (94.7) | 20/22 (90.9)
Peptostreptococcus micros | 13/17 (76.5) | 8/11 (72.7)

a Two cIAI pivotal studies and two Resistant Pathogen studies

b Includes Streptococcus anginosus, Streptococcus intermedius, and Streptococcus constellatus

14.3 Community-Acquired Bacterial Pneumonia

Tigecycline was evaluated in adults for the treatment of community-acquired bacterial pneumonia (CABP) in two randomized, double-blind, active-controlled, multinational, multicenter studies (Studies 1 and 2). These studies compared tigecycline (100 mg intravenous initial dose followed by 50 mg every 12 hours) with levofloxacin (500 mg intravenous every 12 or 24 hours). In one study (Study 1), after at least 3 days of intravenous therapy, a switch to oral levofloxacin (500 mg daily) was permitted for both treatment arms. Total therapy was 7 to 14 days. Patients with community-acquired bacterial pneumonia who required hospitalization and intravenous therapy were enrolled in the studies. The primary efficacy endpoint was the clinical response at the test of cure (TOC) visit in the co-primary populations of the clinically evaluable (CE) and clinical modified intent-to-treat (c-mITT) patients. See Table 8. Clinical cure rates at TOC by pathogen in the microbiologically evaluable patients are presented in Table 9.

Table 8. Clinical Cure Rates from Two Studies in Community-Acquired Bacterial Pneumonia after 7 to 14 Days of Total Therapy

 | Tigecyclinea n/N (%) | Levofloxacinb n/N (%) | 95% CIc
Study 1d
CE | 125/138 (90.6) | 136/156 (87.2) | (-4.4, 11.2)
c-mITT | 149/191 (78) | 158/203 (77.8) | (-8.5, 8.9)
Study 2
CE | 128/144 (88.9) | 116/136 (85.3) | (-5, 12.2)
c-mITT | 170/203 (83.7) | 163/200 (81.5) | (-5.6, 10.1)

a 100 mg initially, followed by 50 mg every 12 hours

b Levofloxacin (500 mg intravenous every 12 or 24 hours)

c 95% confidence interval for the treatment difference

d After at least 3 days of intravenous therapy, a switch to oral levofloxacin (500 mg daily) was permitted for both treatment arms in Study 1.

Table 9. Clinical Cure Rates by Infecting Pathogen in Microbiologically Evaluable Patients with Community-Acquired Bacterial Pneumoniaa

Pathogen | Tigecycline n/N (%) | Levofloxacin n/N (%)
Haemophilus influenzae | 14/17 (82.4) | 13/16 (81.3)
Legionella pneumophila | 10/10 (100.0) | 6/6 (100.0)
Streptococcus pneumoniae (penicillin-susceptible only)b | 44/46 (95.7) | 39/44 (88.6)

a Two CABP studies

b Includes cases of concurrent bacteremia [cure rates of 20/22 (90.9%) versus 13/18 (72.2%) for tigecycline and levofloxacin respectively]

To further evaluate the treatment effect of tigecycline, a post-hoc analysis was conducted in CABP patients with a higher risk of mortality, for whom the treatment effect of antibiotics is supported by historical evidence. The higher-risk group included CABP patients from the two studies with any of the following factors:

- Age ≥ 50 years
- PSI score ≥ 3
- Streptococcus pneumoniae bacteremia

The results of this analysis are shown in Table 10. Age ≥ 50 was the most common risk factor in the higher-risk group.

Table 10. Post-hoc Analysis of Clinical Cure Rates in Patients with Community-Acquired Bacterial Pneumonia Based on Risk of Mortalitya

 | Tigecycline n/N (%) | Levofloxacin n/N (%) | 95% CIb
Study 1c
CE
Higher risk
Yes | 93/103 (90.3) | 84/102 (82.4) | (-2.3, 18.2)
No | 32/35 (91.4) | 52/54 (96.3) | (-20.8, 7.1)
c-mITT
Higher risk
Yes | 111/142 (78.2) | 100/134 (74.6) | (-6.9, 14)
No | 38/49 (77.6) | 58/69 (84.1) | (-22.8, 8.7)
Study 2
CE
Higher risk
Yes | 95/107 (88.8) | 68/85 (80) | (-2.2, 20.3)
No | 33/37 (89.2) | 48/51 (94.1) | (-21.1, 8.6)
c-mITT
Higher risk
Yes | 112/134 (83.6) | 93/120 (77.5) | (-4.2, 16.4)
No | 58/69 (84.1) | 70/80 (87.5) | (-16.2, 8.8)

a Patients at higher risk of death include patients with any one of the following: ≥ 50 years of age; PSI score ≥ 3; or bacteremia due to Streptococcus pneumoniae

b 95% confidence interval for the treatment difference

c After at least 3 days of intravenous therapy, a switch to oral levofloxacin (500 mg daily) was permitted for both treatment arms in Study 1.

16 HOW SUPPLIED/STORAGE AND HANDLING

Tigecycline for injection, USP is supplied in a single dose 10 mL glass vial, containing 50 mg tigecycline lyophilized powder for reconstitution.

Product Code | Unit of Sale | Strength | Each
961110 | NDC 63323-960-10 Unit of 10 | 50 mg per vial | NDC 63323-960-01 10 mL Single Dose Vial

Prior to reconstitution, Tigecycline for injection, USP should be stored at 20° to 25°C (68° to 77°F) [see USP Controlled Room Temperature].

The reconstituted solution of Tigecycline for injection, USP may be stored at room temperature (not to exceed 25°C/77°F) for up to 24 hours (up to 6 hours in the vial and the remaining time in the intravenous bag) [see Dosage and Administration (2.1)].

The container closure is not made with natural rubber latex.

17 PATIENT COUNSELING INFORMATION

- Advise patients, their families, or caregivers that diarrhea is a common problem caused by antibacterial drugs. Sometimes, frequent watery or bloody diarrhea may occur and may be a sign of a more serious intestinal infection. If severe watery or bloody diarrhea develops, tell them to contact his or her healthcare provider [see Warnings and Precautions (5.8)].
- Patients should be counseled that antibacterial drugs including tigecycline should only be used to treat bacterial infections. They do not treat viral infections (e.g., the common cold). When tigecycline is prescribed to treat a bacterial infection, patients should be told that although it is common to feel better early in the course of therapy, the medication should be taken exactly as directed. Skipping doses or not completing the full course of therapy may (1) decrease the effectiveness of the immediate treatment and (2) increase the likelihood that bacteria will develop resistance and will not be treatable by tigecycline or other antibacterial drugs in the future.

Lake Zurich, IL 60047

www.fresenius-kabi.com/us

451320F

PACKAGE LABEL

PACKAGE LABEL - PRINCIPAL DISPLAY - Tigecycline 50 mg Single Dose Vial Label

NDC 63323-960-01 961110

Tigecycline

for Injection, USP

50 mg per vial

For intravenous infusion only.

Preservative Free.

Discard Unused Portion.

Single Dose Vial Rx only

PACKAGE LABEL

PACKAGE LABEL - PRINCIPAL DISPLAY - Tigecycline 50 mg Single Dose Vial Carton Label

NDC 63323-960-10 961110

Tigecycline

for Injection, USP

50 mg per vial

For intravenous infusion only.

Preservative Free.

Discard Unused Portion.

MUST BE FURTHER DILUTED AFTER RECONSTITUTION

AND BEFORE INTRAVENOUS INFUSION

Rx only
10 Single Dose Vials